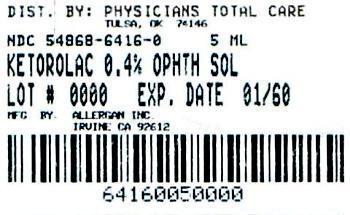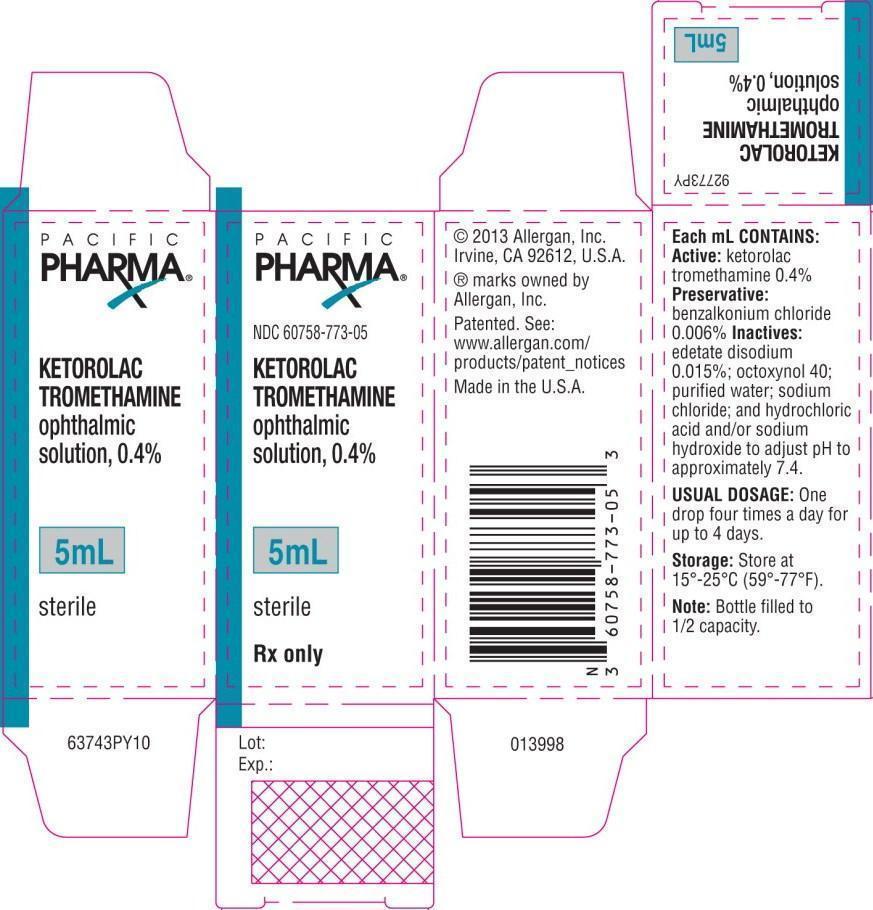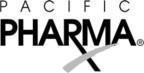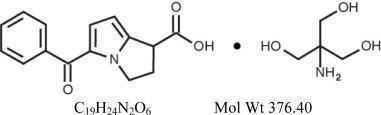 DRUG LABEL: KETOROLAC TROMETHAMINE
NDC: 54868-6416 | Form: SOLUTION/ DROPS
Manufacturer: Physicians Total Care, Inc.
Category: prescription | Type: HUMAN PRESCRIPTION DRUG LABEL
Date: 20150507

ACTIVE INGREDIENTS: Ketorolac Tromethamine 4 mg/1 mL
INACTIVE INGREDIENTS: edetate disodium; octoxynol-40; water; sodium chloride; benzalkonium chloride; hydrochloric acid; sodium hydroxide

KETOROLAC TROMETHAMINE
ophthalmic solution 0.4%
sterile

DESCRIPTION

Ketorolac tromethamine ophthalmic solution 0.4% is a member of the pyrrolo-pyrrole group of nonsteroidal anti-inflammatory drugs (NSAIDs) for ophthalmic use.

Structural and Molecular Formula:

Chemical Name: (±)-5-Benzoyl-2,3-dihydro-1H-pyrrolizine-1-carboxylic acid, compound with 2-amino-2-(hydroxymethyl)-1,3-propanediol (1:1)

Contains: Active: ketorolac tromethamine 0.4%.

Preservative: benzalkonium chloride 0.006%. Inactives: sodium chloride; edetate disodium 0.015%; octoxynol 40; purified water; and hydrochloric acid and/or sodium hydroxide to adjust pH.

Ketorolac tromethamine ophthalmic solution is supplied as a sterile isotonic aqueous 0.4% solution, with a pH of approximately 7.4. Ketorolac tromethamine ophthalmic solution is a racemic mixture of R-(+) and S-(-)- ketorolac tromethamine. Ketorolac tromethamine may exist in three crystal forms. All forms are equally soluble in water. The pKa of ketorolac is 3.5. This white to off-white crystalline substance discolors on prolonged exposure to light. The osmolality of ketorolac tromethamine ophthalmic solution is approximately 290 mOsml/kg.

CLINICAL PHARMACOLOGY

Mechanism of Action

Ketorolac tromethamine is a nonsteroidal anti-inflammatory drug which, when administered systemically, has demonstrated analgesic, anti-inflammatory, and anti-pyretic activity. The mechanism of its action is thought to be due to its ability to inhibit prostaglandin biosynthesis. Ketorolac tromethamine given systemically does not cause pupil constriction.

Pharmacokinetics

One drop (0.05 mL) of 0.5% ketorolac tromethamine ophthalmic solution was instilled into one eye and one drop of vehicle into the other eye TID in 26 normal subjects. Only 5 of 26 subjects had a detectable amount of ketorolac in their plasma (range 10.7 to 22.5 ng/mL) at day 10 during topical ocular treatment. When ketorolac tromethamine 10 mg is administered systemically every 6 hours, peak plasma levels at steady state are around 960 ng/mL.

Clinical Studies

In two double-masked, multi-centered, parallel-group studies, 313 patients who had undergone photorefractive keratectomy received ketorolac tromethamine 0.4% or its vehicle QID for up to 4 days. Significant differences favored ketorolac tromethamine for the reduction of ocular pain and burning/stinging following photorefractive keratectomy surgery.

Results from clinical studies indicate that ketorolac tromethamine has no significant effect upon intraocular pressure.

The safety and effectiveness of ketorolac tromethamine ophthalmic solution in post-cataract surgery patients has not been established.

INDICATIONS AND USAGE

Ketorolac tromethamine ophthalmic solution is indicated for the reduction of ocular pain and burning/stinging following corneal refractive surgery.

CONTRAINDICATIONS

Ketorolac tromethamine ophthalmic solution is contraindicated in patients with previously demonstrated hypersensitivity to any of the ingredients in the formulation.

WARNINGS

There is the potential for cross-sensitivity to acetylsalicylic acid, phenylacetic acid derivatives, and other nonsteroidal anti-inflammatory agents. Therefore, caution should be used when treating individuals who have previously exhibited sensitivities to these drugs.

With some nonsteroidal anti-inflammatory drugs there exists the potential for increased bleeding time due to interference with thrombocyte aggregation. There have been reports that ocularly applied nonsteroidal anti-inflammatory drugs may cause increased bleeding of ocular tissues (including hyphemas) in conjunction with ocular surgery.

PRECAUTIONS

General

All topical nonsteroidal anti-inflammatory drugs (NSAIDs), including ketorolac tromethamine ophthalmic solution, may slow or delay healing. Topical corticosteroids are also known to slow or delay healing. Concomitant use of topical NSAIDs and topical steroids may increase the potential for healing problems.

Use of topical NSAIDs may result in keratitis. In some susceptible patients, continued use of topical NSAIDs may result in epithelial breakdown, corneal thinning, corneal erosion, corneal ulceration or corneal perforation. These events may be sight threatening. Patients with evidence of corneal epithelial breakdown should immediately discontinue use of topical NSAIDs and should be closely monitored for corneal health.

Postmarketing experience with topical NSAIDs suggests that patients with complicated ocular surgeries, corneal denervation, corneal epithelial defects, diabetes mellitus, ocular surface diseases (e.g., dry eye syndrome), rheumatoid arthritis, or repeat ocular surgeries within a short period of time may be at increased risk for corneal adverse events which may become sight threatening. Topical NSAIDs should be used with caution in these patients.

Postmarketing experience with topical NSAIDs also suggests that use more than 24 hours prior to surgery or use beyond 14 days post-surgery may increase patient risk for the occurrence and severity of corneal adverse events.

It is recommended that ketorolac tromethamine ophthalmic solution be used with caution in patients with known bleeding tendencies or who are receiving other medications, which may prolong bleeding time.

Information for Patients

Ketorolac tromethamine ophthalmic solution should not be administered while wearing contact lenses.

Carcinogenesis, Mutagenesis, Impairment of Fertility

Ketorolac tromethamine was neither carcinogenic in rats given up to 5 mg/kg/day orally for 24 months (156 times the maximum recommended human topical ophthalmic dose, on a mg/kg basis, assuming 100% absorption in humans and animals) nor in mice given 2 mg/kg/day orally for 18 months (62.5 times the maximum recommended human topical ophthalmic dose, on a mg/kg basis, assuming 100% absorption in humans and animals).

Ketorolac tromethamine was not mutagenic in vitro in the Ames assay or in forward mutation assays. Similarly, it did not result in an in vitro increase in unscheduled DNA synthesis or an in vivo increase in chromosome breakage in mice. However, ketorolac tromethamine did result in an increased incidence in chromosomal aberrations in Chinese hamster ovary cells.

Ketorolac tromethamine did not impair fertility when administered orally to male and female rats at doses up to 280 and 499 times the maximum recommended human topical ophthalmic dose, respectively, on a mg/kg basis, assuming 100% absorption in humans and animals.

Pregnancy

Teratogenic Effects: Pregnancy Category C

Ketorolac tromethamine, administered during organogenesis, was not teratogenic in rabbits or rats at oral doses up to 112 times and 312 times the maximum recommended human topical ophthalmic dose, respectively, on a mg/kg basis assuming 100% absorption in humans and animals. When administered to rats after Day 17 of gestation at oral doses up to 46 times the maximum recommended human topical ophthalmic dose on a mg/kg basis, assuming 100% absorption in humans and animals, ketorolac tromethamine resulted in dystocia and increased pup mortality. There are no adequate and well-controlled studies in pregnant women. Ketorolac tromethamine ophthalmic solution should be used during pregnancy only if the potential benefit justifies the potential risk to the fetus.

Nonteratogenic Effects

Because of the known effects of prostaglandin-inhibiting drugs on the fetal cardiovascular system (closure of the ductus arteriosus), the use of ketorolac tromethamine ophthalmic solution during late pregnancy should be avoided.

Nursing Mothers

Caution should be exercised when ketorolac tromethamine ophthalmic solution is administered to a nursing woman.

Pediatric Use

Safety and effectiveness of ketorolac tromethamine in pediatric patients below the age of 3 have not been established.

Geriatric Use

No overall differences in safety or effectiveness have been observed between elderly and younger patients.

ADVERSE REACTIONS

The most frequently reported adverse reactions for ketorolac tromethamine ophthalmic solution occurring in approximately 1 to 5% of the overall study population were conjunctival hyperemia, corneal infiltrates, headache, ocular edema and ocular pain.

The most frequent adverse events reported with the use of ketorolac tromethamine ophthalmic solutions have been transient stinging and burning on instillation. These events were reported by 20% - 40% of patients participating in these other clinical trials.

Other adverse events occurring approximately 1% - 10% of the time during treatment with ketorolac tromethamine ophthalmic solutions included allergic reactions, corneal edema, iritis, ocular inflammation, ocular irritation, ocular pain, superficial keratitis, and superficial ocular infections.

Clinical Practice

The following events have been identified during postmarketing use of ketorolac tromethamine ophthalmic solutions in clinical practice. Because they are reported voluntarily from a population of unknown size, estimates of frequency cannot be made. The events, which have been chosen for inclusion due to either their seriousness, frequency of reporting, possible causal connection to topical ketorolac tromethamine ophthalmic solutions, or a combination of these factors, include corneal erosion, corneal perforation, corneal thinning and epithelial breakdown (see PRECAUTIONS, General).

DOSAGE AND ADMINISTRATION

The recommended dose of ketorolac tromethamine ophthalmic solution is one drop four times a day in the operated eye as needed for pain and burning/stinging for up to 4 days following corneal refractive surgery.

Ketorolac tromethamine ophthalmic solution has been safely administered in conjunction with other ophthalmic medications such as antibiotics, beta blockers, carbonic anhydrase inhibitors, cycloplegics, and mydriatics.

HOW SUPPLIED

Ketorolac tromethamine ophthalmic solution 0.4% is supplied sterile in an opaque white LDPE plastic bottle with a white dropper with a gray high impact polystyrene (HIPS) cap as follows:

5 mL in 10 mL bottle - NDC 54868-6416-0

STORAGE AND HANDLING

Storage: Store at 15°-25°C (59°-77°F).

Revised: 10/2013

© 2013 Allergan, Inc., Irvine, CA 92612, U.S.A.
® marks owned by Allergan, Inc.
Patented. See: www.allergan.com/products/patent_notices
Made in the U.S.A.

71654PY10

Distributed by:

Physicians Total Care, Inc.

Tulsa, OK 74146

PACKAGE LABEL

Pacific
Pharma®

NDC 60758-773-05

KETOROLAC
TROMETHAMINE
ophthalmic
solution, 0.4%

5mL

sterile

Rx only

NDC 54868-6416-0

KETOROLAC TROMETHAMINE